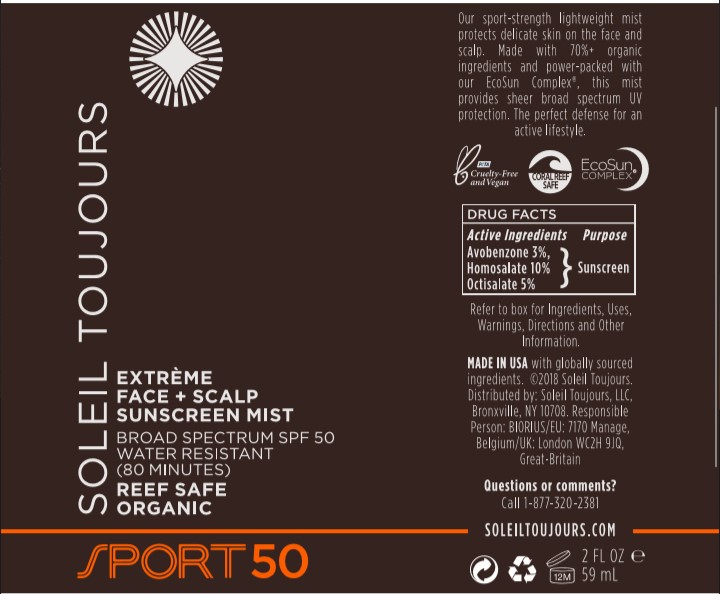 DRUG LABEL: Soleil Tojours
NDC: 58443-0347 | Form: SPRAY
Manufacturer: Prime Enterprises Inc.
Category: otc | Type: HUMAN OTC DRUG LABEL
Date: 20200819

ACTIVE INGREDIENTS: AVOBENZONE 24.99 mg/1 mL; OCTISALATE 41.65 mg/1 mL; HOMOSALATE 83.3 mg/1 mL
INACTIVE INGREDIENTS: ASCORBYL PALMITATE; LEVOMENOL; POLYESTER-8 (1400 MW, CYANODIPHENYLPROPENOYL CAPPED); ALCOHOL; PORPHYRA UMBILICALIS; TETRAHEXYLDECYL ASCORBATE; ISOBORNYL ACRYLATE; DIBUTYL MALEATE; CAMELLIA OLEIFERA LEAF; GLYCERIN; ALPHA-TOCOPHEROL ACETATE; WATER

Soleil Toujours Extreme Face + Scalp Sunscreen Mist SPF50 Broad Spectrum

Active Ingredients

Avobenzone 3.0%

Homosalate 10.0%

Octisalate 5.0%

Uses

- helps prevent sunburn
  - if used as directed with other sun protection measures (see Directions) decreases the risk of skin cancer and early skin aging caused by the sun

Flammable

Do not use near heat, flame or while smoking

Warnings

For external use only

Do not use on damaged or broken skin.

When using this product keep out of eyes. Rinse with water to remove. Keep away from face to avoid breathing it.

Stop use and ask a doctor if rash occurs. Keep away from face to avoid breathing it. Contents under pressure do not puncture or incinerate. Do not store at tempertures above 120 F

Keep out of reach of children. If product is swallowed, get medical help or contact a Poison Control Center right away.

Do not use on damaged or broken skin

When using this product keep out of eyes. Rinse with water to remove.

Stop use and ask a doctor if rash occurs

Keep out of reach of children. If product is swallowed, get medical help or contact a Poison Control Center right away.

INACTIVE INGREDIENTS

Ascorbyl Palmitate, Bisabolol, Camellia Oleifera (Green Tea) Leaf Extract, Glycerin, Polyester-8, Porphyra Umbilicalis Extract, SD Alcohol 40-B, Tetrahexyldecyl Ascorbate, Tocopheryl Acetate, VA/Butyl Maleate/Isobornyl Acrylate Copolymer, Water

Purpose

Sunscreen

Directions

- Shake well before use
- with your eyes completly closed mist face evenly. holding bottle 10-12 inches away from face. Do not breathe mist in. Allow to fully dry.
- Apply liberally 15 minutes beore sun exposure
- reapply:
- after 80 minutes of swimming or sweating
- immediately after towel drying
- at least every 2 hours
- Sun Protection Measures Spending time ine the sun increases your risk of skin cancer and early skin aging. To decrease this risk, regularly use a sunscreen with a broad spectrum SPF valvue of 15 or higher and other sun protecion measures including:
- limit tim ein the sun, especially from 10am-2pm
- wear long sleeve shirts, pants, hats, and sunglasses
- children under 6 months: Ask a doctor

Other Information

- protect the product in this container from excessive heat and direct sunlight.

Questions or Comments?

Call 1-877-320-2381